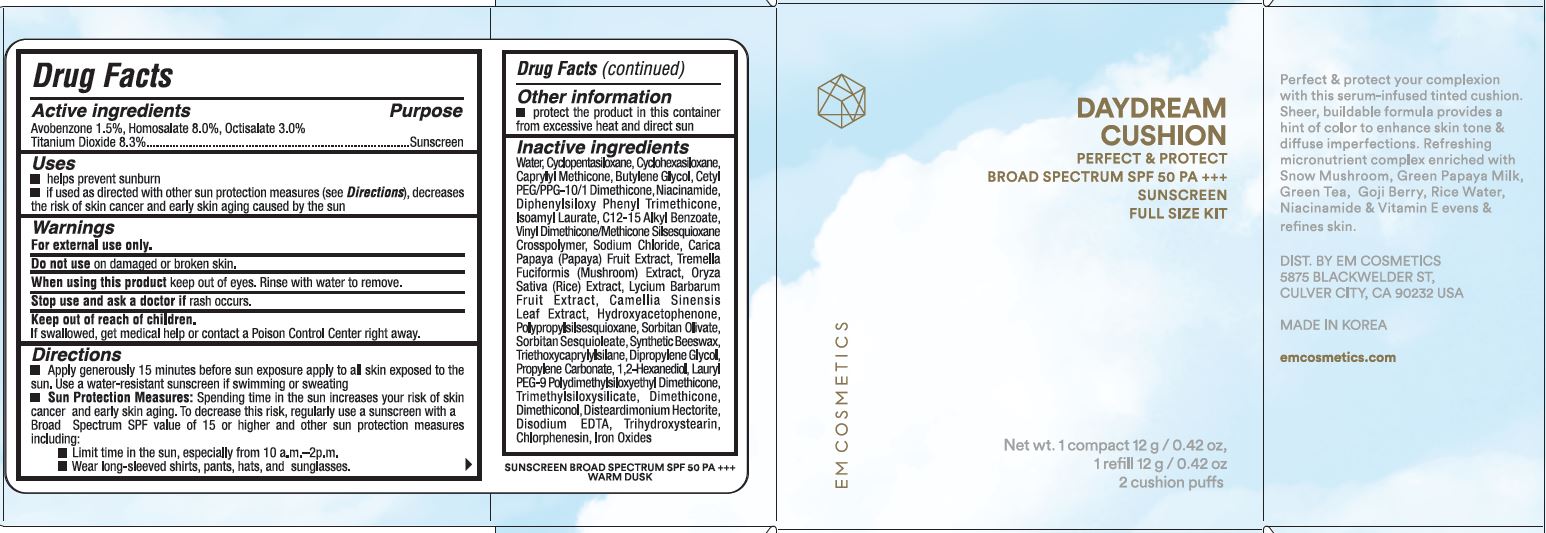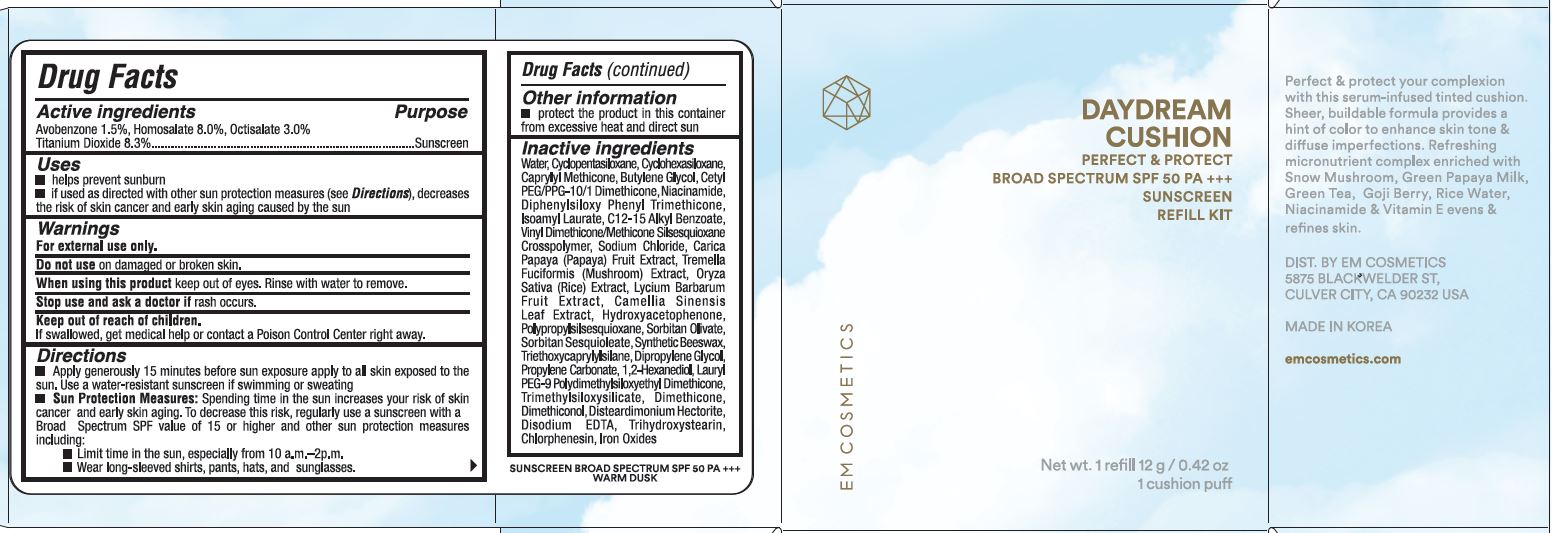 DRUG LABEL: DAYDREAM CUSHION
NDC: 73586-107 | Form: CREAM
Manufacturer: EM Cosmetics LLC
Category: otc | Type: HUMAN OTC DRUG LABEL
Date: 20241129

ACTIVE INGREDIENTS: AVOBENZONE 1.5 g/100 g; HOMOSALATE 8 g/100 g; OCTISALATE 3 g/100 g; TITANIUM DIOXIDE 8.3 g/100 g
INACTIVE INGREDIENTS: DIPHENYLSILOXY PHENYL TRIMETHICONE; ISOAMYL LAURATE; ALKYL (C12-15) BENZOATE; VINYL DIMETHICONE/METHICONE SILSESQUIOXANE CROSSPOLYMER; SODIUM CHLORIDE; PAPAYA; TREMELLA FUCIFORMIS WHOLE; WHITE RICE; LYCIUM BARBARUM FRUIT; GREEN TEA LEAF; HYDROXYACETOPHENONE; TRIMETHYLSILOXYSILICATE (M/Q 1.0-1.2); LAURYL PEG-9 POLYDIMETHYLSILOXYETHYL DIMETHICONE; TRIHYDROXYSTEARIN; PROPYLSILSESQUIOXANE, HYDROGEN TERMINATED; SORBITAN OLIVATE; SORBITAN SESQUIOLEATE; YELLOW WAX; TRIETHOXYCAPRYLYLSILANE; DIPROPYLENE GLYCOL; 1,2-HEXANEDIOL; PROPYLENE CARBONATE; DIMETHICONE; DIMETHICONOL (2000 CST); DISTEARDIMONIUM HECTORITE; EDETATE DISODIUM; CHLORPHENESIN; FERRIC OXIDE RED; WATER; CYCLOMETHICONE 5; CAPRYLYL TRISILOXANE; BUTYLENE GLYCOL; CETYL PEG/PPG-10/1 DIMETHICONE (HLB 1.5); CYCLOMETHICONE 6; NIACINAMIDE

EM COSMETICS - DAYDREAM CUSHION - WARM DUSK - 73586-107

ACTIVE INGREDIENTS

Avobenzone 1.5%

Homosalate 8.0%

Octisalate 3.0%

Titanium Dioxide 8.3%

Purpose

Sunscreen

Purpose

Sunscreen

USES

- Helps prevent sunburn.
- If used as directed with other sun protection measures (see Directions), decreases the risk of skin cancer, early skin aging by the sun.

WARNINGS

For external use only.

Do not use on damaged or broken skin.

When using this product keep out of eyes. Rinse with water to remove.

Stop use and ask a doctor if rash occurs.

Keep out of reach of children. If product is swallowed, get medical help or contact a Poison Control Center right away.

DIRECTIONS

- Apply generously 15 minutes before sun exposure apply to all skin exposed to the sun. Use a water-resistant sunscreen if swimming or sweating.

- Sun Protection Measures: Spending time in the sun increases your risk of skin cancer & early skin aging. To decrease this risk, regularly use a sunscreen with a broad spectrum SPF of 15 or higher and other sun protection measures including:
- limit time in the sun, especially from 10 a.m. - 2 p.m.
- wear long-sleeve shirts, pants, hats, and sunglasses

OTHER INFORMATION

- PROTECT THE PRODUCT IN THIS CONTAINER FROM EXCESSIVE HEAT AND DIRECT SUN

INACTIVE INGREDIENTS

WATER, CYCLOPENTASILOXANE, CAPRYLYL METHICONE, BUTYLENE GLYCOL, CETYL PEG/PPG-10/1 DIMETHICONE, CYCLOHEXASILOXANE, NIACINAMIDE, ISOAMYL LAURATE, DIPHENYLSILOXY PHENYL TRIMETHICONE, C12-15 ALKYL BENZOATE, VINYL DIMETHICONE/METHICONE SILSEQUIOXANE CROSSPOLYMER, SODIUM CHLORIDE, CARICA PAPAYA (PAPAYA) FRUIT EXTRACT, TREMELLA FUCIFORMIS (MUSHROOM) EXTRACT, ORYZA SATIVA (RICE) EXTRACT, LYCIUM BARBARUM FRUIT EXTRACT, CAMELIA SINENSIS LEAF EXTRACT, HYDROXYACETOPHENONE, TRIMETHYLSILOXYSILICATE, LAURYL PEG-9 POLYDIMETHYLSILOXYETHYL DIMETHICONE, TRIHYDROXYSTEARIN, POLYPROPYLSILSESQUIOXANE, SORBITAN OLIVATE, SORBITAN SESQUIOLATE, SYNTHETIC BEESWAX, TRIETHOXYCAPRYLYLSILANE, DIPROPYLENE GLYCOL, 1,2-HEXANEDIOL, PROPYLENE CARBONATE, DIMETHICONE, DIMETHICONAL, DISTEARDIMONIUM HECTORITE, DISODIUM EDTA, CHLORPHENESIN, IRON OXIDES